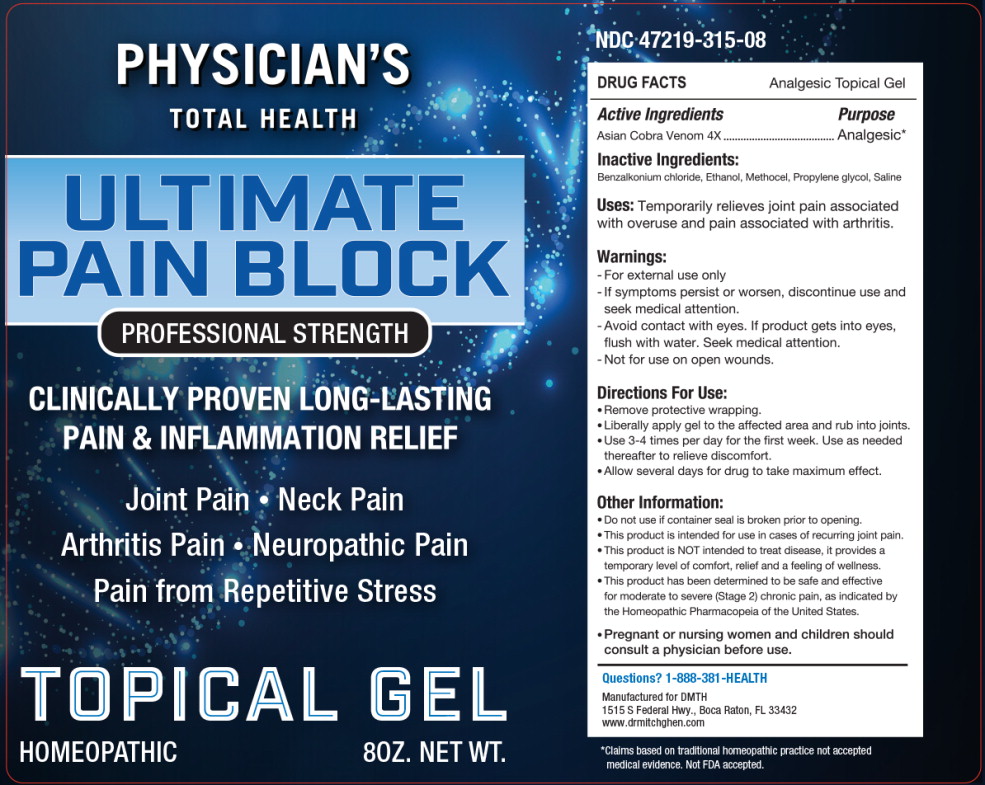 DRUG LABEL: Ultimate Pain Block 

NDC: 47219-315 | Form: GEL
Manufacturer: Nutra Pharma Corporation
Category: homeopathic | Type: HUMAN OTC DRUG LABEL
Date: 20251104

ACTIVE INGREDIENTS: NAJA NAJA VENOM 4 [hp_X]/1 mL
INACTIVE INGREDIENTS: BENZALKONIUM CHLORIDE; ALCOHOL; CARBOXYMETHYLCELLULOSE SODIUM, UNSPECIFIED; PROPYLENE GLYCOL; ISOTONIC SODIUM CHLORIDE SOLUTION

DRUG FACTS Analgesic Topical Gel

Active Ingredients

Asian Cobra Venom 4X

Purpose

Analgesic*

*Claims based on traditional homeopathic practice not accepted medical evidence. Not FDA accepted.

Inactive Ingredients:

Benzalkonium chloride, Ethanol, Methocel, Propylene glycol, Saline

Uses:

Temporarily relieves joint pain associated with overuse and pain associated with arthritis.

Warnings:

- For external use only
- If symptoms persist or worsen, discontinue use and seek medical attention.
- Avoid contact with eyes. If product gets into eyes, flush with water. Seek medical attention.
- Not for use on open wounds.

Directions For Use:

- Remove protective wrapping.
- Liberally apply gel to the affected area and rub into joints.
- Use 3-4 times per day for the first week. Use as needed thereafter to relieve discomfort.
- Allow several days for drug to take maximum effect.

Other Information:

- Do not use if container seal is broken prior to opening.
- This product is intended for use in cases of recurring joint pain.
- This product is NOT intended to treat disease, it provides a temporary level of comfort, relief and a feeling of wellness.
- This product has been determined to be safe and effective for moderate to severe (Stage 2) chronic pain, as indicated by the Homeopathic Pharmacopeia of the United States.

KEEP OUT OF REACH OF CHILDREN

- Pregnant or nursing women and children should consult a physician before use.

Questions?

1-888-381-HEALTH

Principal Display Panel - 8 oz Bottle Label

PHYSICIAN'S
TOTAL HEALTH

ULTIMATE
PAIN BLOCK

PROFESSIONAL STRENGTH

CLINICALLY PROVEN LONG-LASTING
PAIN & INFLAMMATION RELIEF

Joint Pain • Neck Pain
Arthritis Pain • Neuropathic Pain
Pain from Repetitive Stress

TOPICAL GEL

HOMEOPATHIC

8OZ. NET WT.